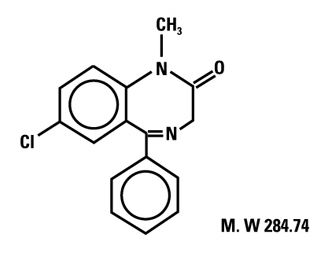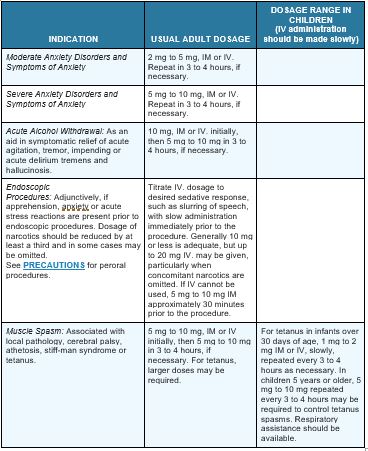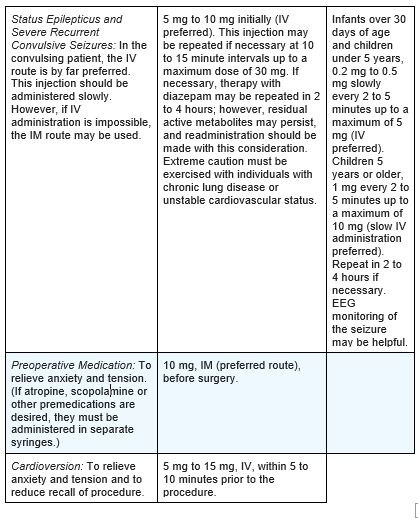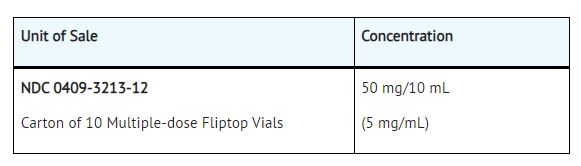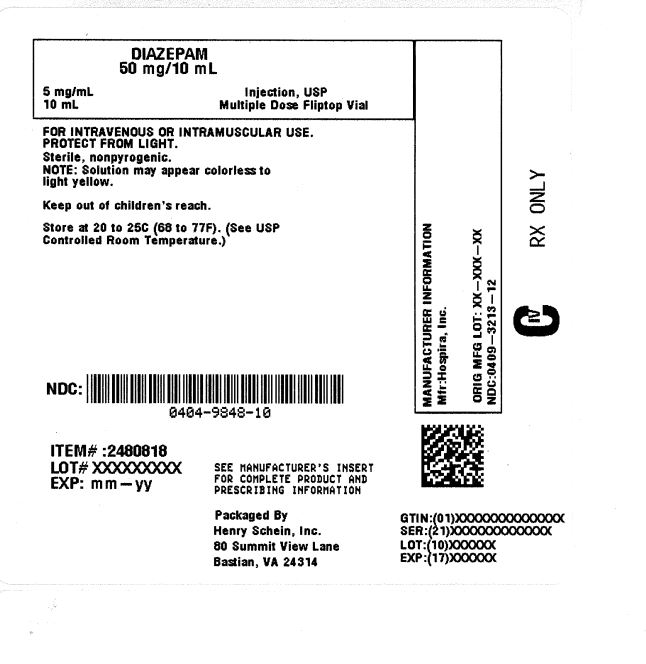 DRUG LABEL: Diazepam
								
NDC: 0404-9848 | Form: INJECTION, SOLUTION
Manufacturer: Henry Schein, Inc.
Category: prescription | Type: HUMAN PRESCRIPTION DRUG LABEL
Date: 20260219
DEA Schedule: CIV

ACTIVE INGREDIENTS: Diazepam 5 mg/1 mL

DIAZEPAM Injection, USP
5mg/mL
Fliptop Vial
Rx only
CIV

BOXED WARNING

WARNING: RISKS FROM CONCOMITANT USE WITH OPIOIDS; ABUSE, MISUSE, AND ADDICTION; AND DEPENDENCE AND WITHDRAWAL REACTIONS
•Concomitant use of benzodiazepines and opioids may result in profound sedation, respiratory depression, coma, and death (see WARNINGS).
•Reserve concomitant prescribing of these drugs in patients for whom alternative treatment options are inadequate.
•Limit dosages and durations to the minimum required.
•Follow patients for signs and symptoms of respiratory depression and sedation (see WARNINGS and PRECAUTIONS).
•The use of benzodiazepines, including diazepam, exposes users to risks of abuse, misuse, and addiction, which can lead to overdose or death. Abuse and misuse of benzodiazepines commonly involve concomitant use of other medications, alcohol, and/or illicit substances, which is associated with an increased frequency of serious adverse outcomes. Before prescribing diazepam and throughout treatment, assess each patient's risk for abuse, misuse, and addiction (see WARNINGS).
•The continued use of benzodiazepines may lead to clinically significant physical dependence. The risks of dependence and withdrawal increase with longer treatment duration and higher daily dose. Although diazepam is indicated only for intermittent use (see INDICATIONS AND USAGE and DOSAGE AND ADMINISTRATION), if used more frequently than recommended, abrupt discontinuation or rapid dosage reduction of diazepam may precipitate acute withdrawal reactions, which can be life-threatening. For patients using diazepam more frequently than recommended, to reduce the risk of withdrawal reactions, use a gradual taper to discontinue diazepam (see WARNINGS).

DESCRIPTION

Diazepam Injection, USP is a sterile, nonpyrogenic solution intended for intramuscular or intravenous administration. Each milliliter (mL) contains 5 mg diazepam; 40% propylene glycol; 10% alcohol; 5% sodium benzoate and benzoic acid added as buffers; and 1.5% benzyl alcohol added as a preservative. pH 6.6 (6.2 to 6.9). Note: Solution may appear colorless to light yellow.

Diazepam is a benzodiazepine derivative chemically designated as 7-chloro-1,3-dihydro-1-methyl-5-phenyl-2H-1,4-benzodiazepin-2-one. It is a colorless crystalline compound, insoluble in water, with the following molecular structure:

CLINICAL PHARMACOLOGY

In animals, diazepam appears to act on parts of the limbic system, the thalamus and hypothalamus, and induces calming effects. Diazepam, unlike chlorpromazine and reserpine, has no demonstrable peripheral autonomic blocking action, nor does it produce extrapyramidal side effects; however, animals treated with diazepam do have a transient ataxia at higher doses. Diazepam was found to have transient cardiovascular depressor effects in dogs. Long-term experiments in rats revealed no disturbances of endocrine function. Injections into animals have produced localized irritation of tissue surrounding injection sites and some thickening of veins after intravenous use.

Population PK analysis in 87 pediatric patients 0.4 – 17.8 years of age with status epilepticus showed that, after initial dosing, the median plasma half-life was 0.5 hours and the median terminal elimination plasma half-life was 18 to 25 hours.

INDICATIONS AND USAGE

Diazepam is indicated for the management of anxiety disorders or for the short-term relief of the symptoms of anxiety. Anxiety or tension associated with the stress of everyday life usually does not require treatment with an anxiolytic.

In acute alcohol withdrawal, diazepam may be useful in the symptomatic relief of acute agitation, tremor, impending or acute delirium tremens and hallucinosis.

As an adjunct prior to endoscopic procedures if apprehension, anxiety or acute stress reactions are present, and to diminish the patient's recall of the procedures. (See WARNINGS.)

Diazepam is a useful adjunct for the relief of skeletal muscle spasm due to reflex spasm to local pathology (such as inflammation of the muscles or joints, or secondary to trauma); spasticity caused by upper motor neuron disorders (such as cerebral palsy and paraplegia); athetosis; stiff-man syndrome; and tetanus.

Diazepam Injection is a useful adjunct in status epilepticus and severe recurrent convulsive seizures.

Diazepam is a useful premedication (the intramuscular route is preferred) for relief of anxiety and tension in patients who are to undergo surgical procedures. Intravenously, prior to cardioversion for the relief of anxiety and tension and to diminish the patient's recall of the procedure.

CONTRAINDICATIONS

Diazepam is contraindicated in patients with a known hypersensitivity to this drug; acute narrow angle glaucoma; and open angle glaucoma unless patients are receiving appropriate therapy.

WARNINGS

Risks from Concomitant Use with Opioids

Concomitant use of benzodiazepines, including diazepam, and opioids may result in profound sedation, respiratory depression, coma, and death. Because of these risks, reserve concomitant prescribing of benzodiazepines and opioids in patients for whom alternative treatment options are inadequate.

Observational studies have demonstrated that concomitant use of opioid analgesics and benzodiazepines increases the risk of drug-related mortality compared to use of opioids alone. If a decision is made to prescribe diazepam concomitantly with opioids, prescribe the lowest effective dosages and minimum durations of concomitant use, and follow patients closely for signs and symptoms of respiratory depression and sedation. Advise both patients and caregivers about the risks of respiratory depression and sedation when diazepam is used with opioids (see PRECAUTIONS; DRUG INTERACTIONS).

Abuse, Misuse, and Addiction

The use of benzodiazepines, including diazepam, exposes users to the risks of abuse, misuse, and addiction, which can lead to overdose or death. Abuse and misuse of benzodiazepines often (but not always) involve the use of doses greater than the maximum recommended dosage and commonly involve concomitant use of other medications, alcohol, and/or illicit substances, which is associated with an increased frequency of serious adverse outcomes, including respiratory depression, overdose, or death (see DRUG ABUSE AND DEPENDENCE; ABUSE).

Before prescribing diazepam and throughout treatment, assess each patient's risk for abuse, misuse, and addiction. Use of diazepam, particularly in patients at elevated risk, necessitates counseling about the risks and proper use of diazepam along with monitoring for signs and symptoms of abuse, misuse, and addiction. Do not exceed the recommended dosing frequency; avoid or minimize concomitant use of CNS depressants and other substances associated with abuse, misuse, and addiction (e.g., opioid analgesics, stimulants); and advise patients on the proper disposal of unused drug. If a substance use disorder is suspected, evaluate the patient and institute (or refer them for) early treatment, as appropriate.

Dependence and Withdrawal Reactions After Use of Diazepam More Frequently Than Recommended

For patients using diazepam more frequently than recommended, to reduce the risk of withdrawal reactions, use a gradual taper to discontinue diazepam (a patient-specific plan should be used to taper the dose).

Patients at an increased risk of withdrawal adverse reactions after benzodiazepine discontinuation or rapid dosage reduction include those who take higher dosages, and those who have had longer durations of use.

Acute Withdrawal Reactions

The continued use of benzodiazepines, including diazepam may lead to clinically significant physical dependence. Although diazepam is indicated only for intermittent use (see INDICATIONS AND USAGE and DOSAGE AND ADMINISTRATION), if used more frequently than recommended, abrupt discontinuation or rapid dosage reduction of diazepam or administration of flumazenil (a benzodiazepine antagonist) may precipitate acute withdrawal reactions, which can be life-threatening (e.g., seizures) (see DRUG ABUSE AND DEPENDENCE; DEPENDENCE).

Protracted Withdrawal Syndrome

In some cases, benzodiazepine users have developed a protracted withdrawal syndrome with withdrawal symptoms lasting weeks to more than 12 months (see DRUG ABUSE AND DEPENDENCE; DEPENDENCE).

When used intravenously, the following procedures should be undertaken to reduce the possibility of venous thrombosis, phlebitis, local irritation, swelling, and, rarely, vascular impairment; the solution should be injected slowly, taking at least one minute for each 5 mg (1 mL) given except for treatment of status epilepticus in children (see DOSAGE AND ADMINISTRATION); do not use small veins, such as those on the dorsum of the hand or wrist; extreme care should be taken to avoid intra-arterial administration or extravasation.

Do not mix or dilute diazepam with other solutions or drugs in syringe or infusion container. If it is not feasible to administer diazepam directly intravenous., it may be injected slowly through the infusion tubing as close as possible to the vein insertion.

Extreme care must be used in administering Diazepam Injection, particularly by the intravenous route, to the elderly, to very ill patients and to those with limited pulmonary reserve because of the possibility that apnea and/or cardiac arrest may occur. Concomitant use of barbiturates, alcohol or other central nervous system depressants increases depression with increased risk of apnea. Resuscitative equipment including that necessary to support respiration should be readily available.

When diazepam is used with a narcotic analgesic, the dosage of the narcotic should be reduced by at least one-third and administered in small increments. In some cases the use of a narcotic may not be necessary.

Diazepam Injection should not be administered to patients in shock, coma, or in acute alcoholic intoxication with depression of vital signs. As is true of most CNS-acting drugs, patients receiving diazepam should be cautioned against engaging in hazardous occupations requiring complete mental alertness, such as operating machinery or driving a motor vehicle.

Tonic status epilepticus has been precipitated in patients treated with intravenous diazepam for petit mal status or petit mal variant status.

Neonatal Sedation and Withdrawal Syndrome

Use of Diazepam injection late in pregnancy can result in sedation (respiratory depression, lethargy, hypotonia) and/or withdrawal symptoms (hyperreflexia, irritability, restlessness, tremors, inconsolable crying, and feeding difficulties) in the neonate (see PRECAUTIONS; PREGNANCY). Monitor neonates exposed to Diazepam injection during pregnancy or labor for signs of sedation and monito

Pediatric Use

Efficacy and safety of parenteral diazepam has not been established in the neonate (30 days or less of age).

Prolonged central nervous system depression has been observed in neonates, apparently due to inability to biotransform diazepam into inactive metabolites.

In pediatric use for the treatment of status epilepticus, in order to obtain maximal clinical effect with the minimum amount of drug and thus to reduce the risk of hazardous side effects, such as apnea or prolonged periods of somnolence, it is recommended that the drug be given as a slow intravenous push over 1 minute (see DOSAGE AND ADMINISTRATION). The safety and tolerability of the recommended dosage regimen is supported by a randomized, double-blind study that included 162 pediatric patients ages 3 months to 17 years who received intravenous diazepam for the treatment of status epilepticus. In this study, 16% of pediatric patients who received diazepam experienced severe or life-threatening respiratory depression.

Benzyl alcohol has been reported to be associated with a fatal gasping syndrome in premature infants.

PRECAUTIONS

General

Although seizures may be brought under control promptly, a significant proportion of patients experience a return to seizure activity, presumably due to the short-lived effect of diazepam after intravenous administration. The physician should be prepared to readminister the drug. However, diazepam is not recommended for maintenance, and once seizures are brought under control, consideration should be given to the administration of agents useful in longer term control of seizures.

The usual precautions in treating patients with impaired hepatic function should be observed. Metabolites of diazepam are excreted by the kidney; to avoid their excess accumulation, caution should be exercised in the administration to patients with compromised kidney function. Since an increase in cough reflex and laryngospasm may occur with peroral endoscopic procedures, the use of a topical anesthetic agent, and the availability of necessary countermeasures are recommended.

Propylene glycol toxicity has been reported in patients treated with diazepam injection at doses significantly greater than recommended. In these cases, diazepam was being used to treat alcohol withdrawal symptoms at doses greater than 900 mg/day. Propylene glycol toxicity is associated with an anion gap metabolic acidosis, serum hyperosmolality, and increased lactate. Propylene glycol toxicity can cause acute tubular necrosis (which can progress to multi-organ failure), mental status changes, hypotension, seizures, and cardiac arrhythmias. Patients at high risk for propylene glycol toxicity include those with renal dysfunction, hepatic dysfunction, impaired alcohol dehydrogenase enzymes, or other comorbidities (such as a history of alcoholism). Until additional information is available, diazepam injection is not recommended for obstetrical use. Lower doses (usually 2 mg to 5 mg) should be used for elderly and debilitated patients.

Risks from Concomitant Use with Opioids

Advise both patients and caregivers about the risks of potentially fatal respiratory depression and sedation when diazepam is used with opioids and not to use such drugs concomitantly unless supervised by a health care provider. Advise patients not to drive or operate heavy machinery until the effects of concomitant use with the opioid have been determined (see WARNINGS; RISKS FROM CONCOMITANT USE WITH OPIOIDS and PRECAUTIONS; DRUG INTERACTIONS)

Abuse, Misuse, and Addiction

Inform patients that the use of diazepam more frequently than recommended, even at recommended dosages, exposes users to risks of abuse, misuse, and addiction, which can lead to overdose and death, especially when used in combination with other medications (e.g., opioid analgesics), alcohol, and/or illicit substances. Inform patients about the signs and symptoms of benzodiazepine abuse, misuse, and addiction; to seek medical help if they develop these signs and/or symptoms; and on the proper disposal of unused drug (see WARNINGS and DRUG ABUSEAND DEPENDENCE)

Withdrawal Reactions

Inform patients that use of diazepam more frequently than recommended may lead to clinically significant physical dependence and that abrupt discontinuation or rapid dosage reduction of diazepam may precipitate acute withdrawal reactions, which can be life-threatening. Inform patients that in some cases, patients taking benzodiazepines have developed a protracted withdrawal syndrome with withdrawal symptoms lasting weeks to more than 12 months (see WARNINGS and DRUG ABUSE AND DEPENDENCE).

Pregnancy

Advise pregnant females that use of Diazepam Injection late in pregnancy can result in sedation (respiratory depression, lethargy, hypotonia) and/or withdrawal symptoms (hyperreflexia, irritability, restlessness, tremors, inconsolable crying, and feeding difficulties) in newborns (see WARNINGS; NEONATAL SEDATION AND WITHDRAWAL SYNDROME and PRECAUTIONS; PREGNANCY). Instruct patients to inform their healthcare provider if they are pregnant.

Advise patients that there is a pregnancy exposure registry that monitors pregnancy outcomes in women exposed to Diazepam Injection during pregnancy (see PRECAUTIONS; PREGNANCY)

Nursing

Advise patients that breastfeeding is not recommended during treatment with Diazepam Injection (see PRECAUTIONS; NURSING MOTHERS)

Drug Interactions

The concomitant use of benzodiazepines and opioids increases the risk of respiratory depression because of actions at different receptor sites in the CNS that control respiration. Benzodiazepines interact at GABAA sites and opioids interact primarily at mµ receptors. When benzodiazepines and opioids are combined, the potential for benzodiazepines to significantly worsen opioid-related respiratory depression exists. Limit dosage and duration of concomitant use of benzodiazepines and opioids, and monitor patients closely for respiratory depression and sedation.

If diazepam is to be combined with other psychotropic agents or anticonvulsant drugs, careful consideration should be given to the pharmacology of the agents to be employed—particularly with known compounds which may potentiate the action of diazepam, such as phenothiazines, narcotics, barbiturates, MAO inhibitors and other antidepressants. In highly anxious patients with evidence of accompanying depression, particularly those who may have suicidal tendencies, protective measures may be necessary.

Diazepam injection has produced hypotension or muscular weakness in some patients particularly when used with narcotics, barbiturates or alcohol.

The clearance of diazepam and certain other benzodiazepines can be delayed in association with cimetidine administration. The clinical significance of this is unclear.

Pregnancy

Pregnancy Exposure Registry

There is a pregnancy exposure registry that monitors pregnancy outcomes in women exposed to AEDs, such as Diazepam injection, during pregnancy. Healthcare providers are encouraged to recommend that pregnant patient taking Diazepam injection enroll in the NAAED Pregnancy Registry by calling 1-888- 233-2334 or online at HTTP://WWW.AEDPREGNANCYREGISTRY.ORG/.

Risk Summary

Neonates born to mothers using benzodiazepines late in pregnancy have been reported to experience symptoms of sedation and/or neonatal withdrawal (see WARNINGS; NEONATAL SEDATION AND WITHDRAWAL SYNDROME, and PRECAUTIONS; CLINICAL CONSIDERATIONS). Available data from published observational studies of pregnant women exposed to benzodiazepines do not report a clear association with benzodiazepines and major birth defects (see DATA).

The background risk of major birth defects and miscarriage for the indicated population is unknown. All pregnancies have a background risk of birth defect, loss, or other adverse outcomes. In the U.S. general population, the estimated risk of major birth defects and of miscarriage in clinically recognized pregnancies is 2% to 4% and 15% to 20%, respectively.

Clinical Considerations

Fetal/Neonatal Adverse Reactions

Benzodiazepines cross the placenta and may produce respiratory depression, hypotonia, and sedation in neonates. Monitor neonates exposed to Diazepam injection during pregnancy or labor for signs of sedation, respiratory depression, hypotonia, and feeding problems. Monitor neonates exposed to Diazepam injection during pregnancy for signs of withdrawal. Manage these neonates accordingly (see WARNINGS; NEONATAL SEDATION AND WITHDRAWAL SYNDROME).

Data

Human Data

Published data from observational studies on the use of benzodiazepines during pregnancy do not report a clear association with benzodiazepines and major birth defects.

Although early studies reported an increased risk of congenital malformations with diazepam and chlordiazepoxide, there was no consistent pattern noted. In addition, the majority of more recent case-control and cohort studies of benzodiazepine use during pregnancy, which were adjusted for confounding exposures to alcohol, tobacco and other medications, have not confirmed these findings.

Animal Data

Diazepam has been shown to produce increased incidences of fetal malformations in mice and hamsters when given orally at single doses of 100 mg/kg or greater (approximately 20 times the maximum recommended adult dose [0.4 mg/kg/day] or greater on a mg/m2 basis). Cleft palate and exencephaly are the most common and consistently reported malformations produced in these species by administration of high, maternally-toxic doses of diazepam during organogenesis. In published animal studies, administration of benzodiazepines or other drugs that enhance GABAergic inhibition to neonatal rats has been reported to result in widespread apoptotic neurodegeneration in the developing brain at plasma concentrations relevant for seizure control in humans. The window of vulnerability to these changes in rats (postnatal days 0-14) includes a period of brain development that takes place during the third trimester of pregnancy in humans.

Nursing Mothers

Risk Summary

Diazepam is present in breastmilk. There are reports of sedation, poor feeding and poor weight gain in infants exposed to benzodiazepines through breast milk. There are no data on the effects of diazepam on milk production. The developmental and health benefits of breastfeeding should be considered along with the mother's clinical need for Diazepam injection and any potential adverse effects on the breastfed infant from Diazepam injection or from the underlying maternal condition.

Clinical Considerations

Infants exposed to Diazepam injection through breast milk should be monitored for sedation, poor feeding and poor weight gain

ADVERSE REACTIONS

Side effects most commonly reported were drowsiness, fatigue and ataxia; venous thrombosis and phlebitis at the site of injection. Other adverse reactions less frequently reported include:

CNS: confusion, depression [including respiratory depression (see WARNINGS; Pediatric Use)], dysarthria, headache, hypoactivity, slurred speech, syncope, tremor, vertigo.

G.I.: constipation, nausea.

G.U.: incontinence, changes in libido, urinary retention.

Cardiovascular: bradycardia, cardiovascular collapse, hypotension.

EENT: blurred vision, diplopia, nystagmus.

Skin: urticaria, skin rash.

Other: hiccups, changes in salivation, neutropenia, jaundice. Paradoxical reactions such as acute hyperexcited states, anxiety, hallucinations, increased muscle spasticity, insomnia, rage, sleep disturbances and stimulation have been reported; should these occur, use of the drug should be discontinued. Minor changes in EEG patterns, usually low-voltage fast activity, have been observed in patients during and after diazepam therapy and are of no known significance.

In peroral endoscopic procedures, coughing, depressed respiration, dyspnea, hyperventilation, laryngospasm and pain in throat or chest have been reported.

Because of isolated reports of neutropenia and jaundice, periodic blood counts and liver function tests are advisable during long-term therapy.

DRUG ABUSE AND DEPENDENCE

Controlled Substance

Diazepam Injection is a schedule IV controlled substance.

Abuse

Diazepam is a benzodiazepine and a CNS depressant with a potential for abuse and addiction. Abuse is the intentional, non-therapeutic use of a drug, even once, for its desirable psychological or physiological effects. Misuse is the intentional use, for therapeutic purposes, of a drug by an individual in a way other than prescribed by a health care provider or for whom it was not prescribed. Drug addiction is a cluster of behavioral, cognitive, and physiological phenomena that may include a strong desire to take the drug, difficulties in controlling drug use (e.g., continuing drug use despite harmful consequences, giving a higher priority to drug use than other activities and obligations), and possible tolerance or physical dependence. Even taking benzodiazepines as prescribed may put patients at risk for abuse and misuse of their medication. Abuse and misuse of benzodiazepines may lead to addiction.

Abuse and misuse of benzodiazepines often (but not always) involve the use of doses greater than the maximum recommended dosage and commonly involve concomitant use of other medications, alcohol, and/or illicit substances, which is associated with an increased frequency of serious adverse outcomes, including respiratory depression, overdose, or death. Benzodiazepines are often sought by individuals who abuse drugs and other substances, and by individuals with addictive disorders (see WARNINGS; ABUSE, MISUSE, AND ADDICTION).

The following adverse reactions have occurred with benzodiazepine abuse and/or misuse: abdominal pain, amnesia, anorexia, anxiety, aggression, ataxia, blurred vision, confusion, depression, disinhibition, disorientation, dizziness, euphoria, impaired concentration and memory, indigestion, irritability, muscle pain, slurred speech, tremors, and vertigo.

The following severe adverse reactions have occurred with benzodiazepine abuse and/or misuse: delirium, paranoia, suicidal ideation and behavior, seizures, coma, breathing difficulty, and death. Death is more often associated with polysubstance use (especially benzodiazepines with other CNS depressants such as opioids and alcohol).

Dependence

Physical Dependence After Use of Diazepam More Frequently Than Recommended

Diazepam may produce physical dependence if used more frequently than recommended. Physical dependence is a state that develops as a result of physiological adaptation in response to repeated drug use, manifested by withdrawal signs and symptoms after abrupt discontinuation or a significant dose reduction of a drug. Although diazepam is indicated only for intermittent use (see INDICATIONS AND USAGE and DOSAGE ANDADMINISTRATION), if used more frequently than recommended, abrupt discontinuation or rapid dosage reduction or administration of flumazenil, a benzodiazepine antagonist, may precipitate acute withdrawal reactions, including seizures, which can be life-threatening. Patients at an increased risk of withdrawal adverse reactions after benzodiazepine discontinuation or rapid dosage reduction include those who take higher dosages (i.e., higher and/or more frequent doses) and those who have had longer durations of use (see WARNINGS; DEPENDENCE AND WITHDRAWAL REACTIONS).

For patients using diazepam more frequently than recommended, to reduce the risk of withdrawal reactions, use a gradual taper to discontinue diazepam (see WARNINGS; DEPENDENCE AND WITHDRAWAL REACTIONS).

Acute Withdrawal Signs and Symptoms

Acute withdrawal signs and symptoms associated with benzodiazepines have included abnormal involuntary movements, anxiety, blurred vision, depersonalization, depression, derealization, dizziness, fatigue, gastrointestinal adverse reactions (e.g., nausea, vomiting, diarrhea, weight loss, decreased appetite), headache, hyperacusis, hypertension, irritability, insomnia, memory impairment, muscle pain and stiffness, panic attacks, photophobia, restlessness, tachycardia, and tremor. More severe acute withdrawal signs and symptoms, including life-threatening reactions, have included catatonia, convulsions, delirium tremens, depression, hallucinations, mania, psychosis, seizures, and suicidality.

Protracted Withdrawal Syndrome

Protracted withdrawal syndrome associated with benzodiazepines is characterized by anxiety, cognitive impairment, depression, insomnia, formication, motor symptoms (e.g., weakness, tremor, muscle twitches), paresthesia, and tinnitus that persists beyond 4 to 6 weeks after initial benzodiazepine withdrawal. Protracted withdrawal symptoms may last weeks to more than 12 months. As a result, there may be difficulty in differentiating withdrawal symptoms from potential re-emergence or continuation of symptoms for which the benzodiazepine was being used.

Tolerance

Tolerance to diazepam may develop after use more frequently than recommended. Tolerance is a physiological state characterized by a reduced response to a drug after repeated administration (i.e., a higher dose of a drug is required to produce the same effect that was once obtained at a lower dose).

Tolerance to the therapeutic effect of benzodiazepines may develop; however, little tolerance develops to the amnestic reactions and other cognitive impairments caused by benzodiazepines.

OVERDOSAGE

Overdosage of benzodiazepines is characterized by central nervous system depression ranging from drowsiness to coma. In mild to moderate cases, symptoms can include drowsiness, confusion, dysarthria, lethargy, hypnotic state, diminished reflexes, ataxia, and hypotonia. Rarely, paradoxical or disinhibitory reactions (including agitation, irritability, impulsivity, violent behavior, confusion, restlessness, excitement, and talkativeness) may occur. In severe overdosage cases, patients may develop respiratory depression and coma. Overdosage of benzodiazepines in combination with other CNS depressants (including alcohol and opioids) may be fatal (see WARNINGS; ABUSE, MISUSE, AND ADDICTION). Markedly abnormal (lowered or elevated) blood pressure, heart rate, or respiratory rate raise the concern that additional drugs and/or alcohol are involved in the overdosage.

In managing benzodiazepine overdosage, employ general supportive measures, including intravenous fluids and airway maintenance. Flumazenil, a specific benzodiazepine receptor antagonist indicated for the complete or partial reversal of the sedative effects of benzodiazepines in the management of benzodiazepine overdosage, can lead to withdrawal and adverse reactions, including seizures, particularly in the context of mixed overdosage with drugs that increase seizure risk (e.g., tricyclic and tetracyclic antidepressants) and in patients with long-term benzodiazepine use and physical dependency. The risk of withdrawal seizures with flumazenil use may be increased in patients with epilepsy. Flumazenil is contraindicated in patients who have received a benzodiazepine for control of a potentially life-threatening condition (e.g., status epilepticus). If the decision is made to use flumazenil, it should be used as an adjunct to, not as a substitute for, supportive management of benzodiazepine overdosage. See the flumazenil injection Prescribing Information.

Consider contacting a poison center (1-800-222-1222), POISONCONTROL.ORG, or a medical toxicologist for additional overdosage management recommendations.

DOSAGE AND ADMINISRATION

Dosage should be individualized for maximum beneficial effect. The usual recommended dose in older children and adults ranges from 2 mg to 20 mg intramuscular or intravenous, depending on the indication and its severity. In some conditions, e.g., tetanus, larger doses may be required. (See dosage for specific indications.) In acute conditions the injection may be repeated within one hour although an interval of 3 to 4 hours is usually satisfactory. Lower doses (usually 2 mg to 5 mg) and slow increase in dosage should be used for elderly or debilitated patients and when other sedative drugs are administered. (See WARNINGS and ADVERSE REACTIONS.)

For dosage in infants above the age of 30 days and children, see the specific indications below. When intravenous use is indicated, facilities for respiratory assistance should be readily available.

Intramuscular: Diazepam Injection, USP should be injected deeply into the muscle.

Intravenous Use: For the treatment of status epilepticus in children, the solution should be injected slowly, taking one minute for administration (See WARNINGS, particularly for use in children.). For other indications, the solution should be injected slowly taking at least one minute for each 5 mg (1 mL) given. Do not use small veins, such as those on the dorsum of the hand or wrist. Extreme care should be taken to avoid intra-arterial administration or extravasation.

Do not mix or dilute diazepam with other solutions or drugs in syringe or infusion container. If it is not feasible to administer diazepam directly intravenous., it may be injected slowly through the infusion tubing as close as possible to the vein insertion.

Once the acute symptomatology has been properly controlled with diazepam injection, the patient may be placed on oral therapy with diazepam if further treatment is required.

Parenteral drug products should be inspected visually for particulate matter and discoloration prior to administration, whenever solution and container permit.

NOTE: Solution may appear colorless to light yellow.

HOW SUPPLIED

Diazepam Injection, USP is supplied as follows:

Store at 20 to 25°C (68 to 77°F). [See USP Controlled Room Temperature.]

Protect from light.

Product repackaged by: Henry Schein, Inc., Bastian, VA 24314
From Original Manufacturer/Distributor's NDC and Unit of Sale | To Henry Schein Repackaged Product NDC and Unit of Sale | Total Strength/Total Volume (Concentration) per unit
NDC 0409-3213-12 Box of 10 Fliptop Vial | NDC 0404-9848-10 1 10 mL multiple dose vial in a bag (Vial bears NDC 0409-3213-11) | 50 mg (5 mg/mL)

ANIMAL PHARMACOLOGY

Oral LD50 of diazepam is 720 mg/kg in mice and 1,240 mg/kg in rats. Intraperitoneal administration of 400 mg/kg to a monkey resulted in death on the sixth day.

Reproduction Studies

A series of rat reproduction studies was performed with diazepam in oral doses of 1, 10, 80 and 100 mg/kg given for periods ranging from 60 to 228 days prior to mating. At 100 mg/kg there was a decrease in the number of pregnancies and surviving offspring in these rats. These effects may be attributable to prolonged sedative activity, resulting in lack of interest in mating and lessened maternal nursing and care of the young. Neonatal survival of rats at doses lower than 100 mg/kg was within normal limits. Several neonates, both controls and experimentals, in these rat reproduction studies showed skeletal or other defects. Further studies in rats at doses up to and including 80 mg/kg/day did not reveal significant teratological effects on the offspring. Rabbits were maintained on doses of 1, 2, 5 and 8 mg/kg from day 6 through day 18 of gestation. No adverse effects on reproduction and no teratological changes were noted.

CAUTION: Federal (USA) law prohibits dispensing without prescription.

This product's labeling may have been updated. For the most recent prescribing information, please visit WWW.PFIZER.COM.

Distributed by Hospira, Inc., Lake Forest, IL 60045 USA

LAB-0837-7.0
Revised: April 2023